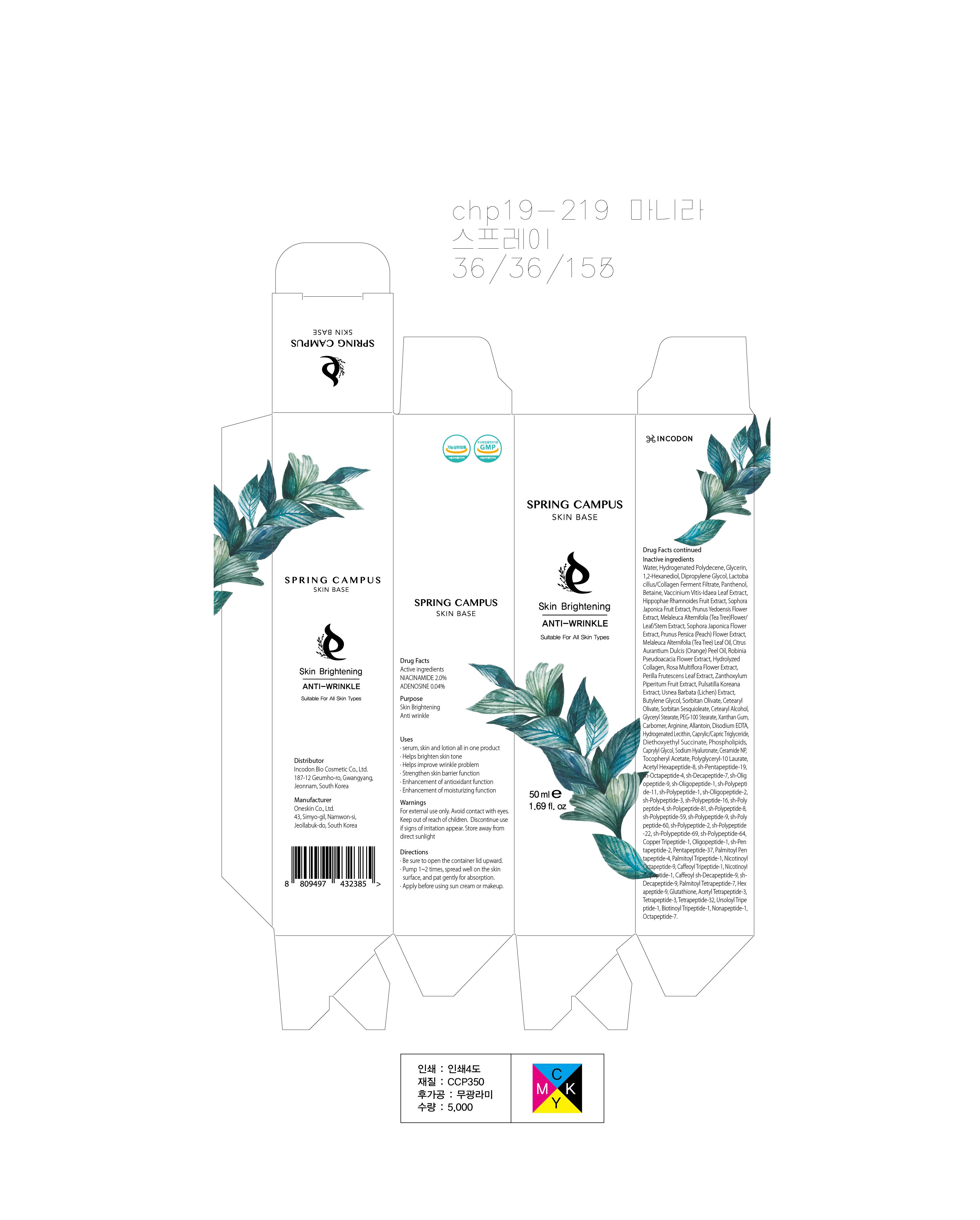 DRUG LABEL: Spring Campus Skin Base
NDC: 82074-020 | Form: LIQUID
Manufacturer: INCODON BIOCOSMETIC Co., Ltd.
Category: otc | Type: HUMAN OTC DRUG LABEL
Date: 20210702

ACTIVE INGREDIENTS: NIACINAMIDE 1.0 g/50 mL; ADENOSINE 0.02 g/50 mL
INACTIVE INGREDIENTS: Water; Glycerin; 1,2-Hexanediol

ACTIVE INGREDIENTS

NIACINAMIDE 2.0%
ADENOSINE 0.04%

INACTIVE INGREDIENTS

Water, Hydrogenated Polydecene, Glycerin, 1,2-Hexanediol, Dipropylene Glycol, Lactobacillus/Collagen Ferment Filtrate, Panthenol, Betaine, Vaccinium Vitis-Idaea Leaf Extract, Hippophae Rhamnoides Fruit Extract, Sophora Japonica Fruit Extract, Prunus Yedoensis Flower Extract, Melaleuca Alternifolia (Tea Tree)Flower/Leaf/Stem Extract, Sophora Japonica Flower Extract, Prunus Persica (Peach) Flower Extract, Melaleuca Alternifolia (Tea Tree) Leaf Oil, Citrus Aurantium Dulcis (Orange) Peel Oil, Robinia Pseudoacacia Flower Extract, Hydrolyzed Collagen, Rosa Multiflora Flower Extract, Perilla Frutescens Leaf Extract, Zanthoxylum Piperitum Fruit Extract, Pulsatilla Koreana Extract, Usnea Barbata (Lichen) Extract, Butylene Glycol, Sorbitan Olivate, Cetearyl Olivate, Sorbitan Sesquioleate, Cetearyl Alcohol, Glyceryl Stearate, PEG-100 Stearate, Xanthan Gum, Carbomer, Arginine, Allantoin, Disodium EDTA, Hydrogenated Lecithin, Caprylic/Capric Triglyceride, Diethoxyethyl Succinate, Phospholipids, Caprylyl Glycol, Sodium Hyaluronate, Ceramide NP, Tocopheryl Acetate, Polyglyceryl-10 Laurate, Acetyl Hexapeptide-8, sh-Pentapeptide-19, sh-Octapeptide-4, sh-Decapeptide-7, sh-Oligopeptide-9, sh-Oligopeptide-1, sh-Polypeptide-11, sh-Polypeptide-1, sh-Oligopeptide-2, sh-Polypeptide-3, sh-Polypeptide-16, sh-Polypeptide-4, sh-Polypeptide-81, sh-Polypeptide-8, sh-Polypeptide-59, sh-Polypeptide-9, sh-Polypeptide-60, sh-Polypeptide-2, sh-Polypeptide-22, sh-Polypeptide-69, sh-Polypeptide-64, Copper Tripeptide-1, Oligopeptide-1, sh-Pentapeptide-2, Pentapeptide-37, Palmitoyl Pentapeptide-4, Palmitoyl Tripeptide-1, Nicotinoyl Octapeptide-9, Caffeoyl Tripeptide-1, Nicotinoyl-Tripeptide-1, Caffeoyl sh-Decapeptide-9, sh-Decapeptide-9, Palmitoyl Tetrapeptide-7, Hexapeptide-9, Glutathione, Acetyl Tetrapeptide-3, Tetrapeptide-3, Tetrapeptide-32, Ursoloyl Tripeptide-1, Biotinoyl Tripeptide-1, Nonapeptide-1, Octapeptide-7.

PURPOSE

Skin Brightening
Anti wrinkle

WARNINGS

For external use only. Avoid contact with eyes. Keep out of reach of children. Discontinue use if signs of irritation appear. Store away from direct sunlight

KEEP OUT OF REACH OF CHILDREN

Uses

■ Serum, skin and lotion all in one product
■ Helps brighten skin tone
■ Helps improve wrinkle problem
■ Strengthen skin barrier function
■ Enhancement of antioxidant function
■ Enhancement of moisturizing function

Directions

■ Be sure to open the container lid upward.
■ Pump 1~2 times, spread well on the skin surface, and pat gently for absorption.
■ Apply before using sun cream or makeup.